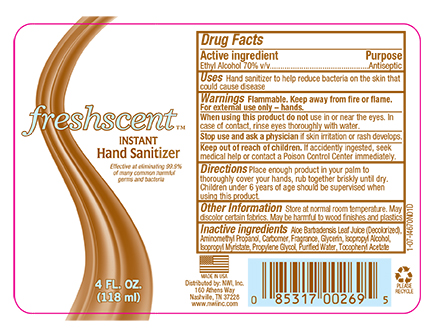 DRUG LABEL: Instant Hand Sanitizer
NDC: 51824-020 | Form: GEL
Manufacturer: New World Imports, Inc.
Category: otc | Type: HUMAN OTC DRUG LABEL
Date: 20251202

ACTIVE INGREDIENTS: ALCOHOL 0.7 mL/1 mL
INACTIVE INGREDIENTS: GLYCERIN; ISOPROPYL ALCOHOL; ISOPROPYL MYRISTATE; PROPYLENE GLYCOL; WATER; .ALPHA.-TOCOPHEROL ACETATE; ALOE VERA LEAF; AMINOMETHYLPROPANOL; CARBOMER 940

Instant Hand Sanitizer

Active ingredient

Ethyl Alcohol 70% v/v

Purpose

Antiseptic

Uses

Hand sanitizer to help reduce bacteria on the skin that could cause disease

Warnings

Flammable. Keep away from fire or flame. For external use only – hands.

When using this product do notuse in or near the eyes. In case of contact, rinse eyes thoroughly with water.

Stop use and ask a physicianif skin irritation or rash develops.

Keep out of reach of children.If accidently ingested, seek medical help or contact a Poison Control Center immediately.

Directions

Place enough product in your palm to thoroughly cover your hands, rub together briskly until dry. Children under 6 years of age should be supervised when using this product.

Other Information

Store at normal room temperature. May discolor certain fabrics. May be harmful to wood finishes and plastics

Inactive ingredients

Aloe Barbadenis Leaf Juice (Decolorized), Aminomethyl Propanol, Carbomer, Fragrance, Glycerin, Isopropyl Alcohol, Isopropyl Myristate, Propylene Glycol, Purified Water, Tocopheryl Acetate